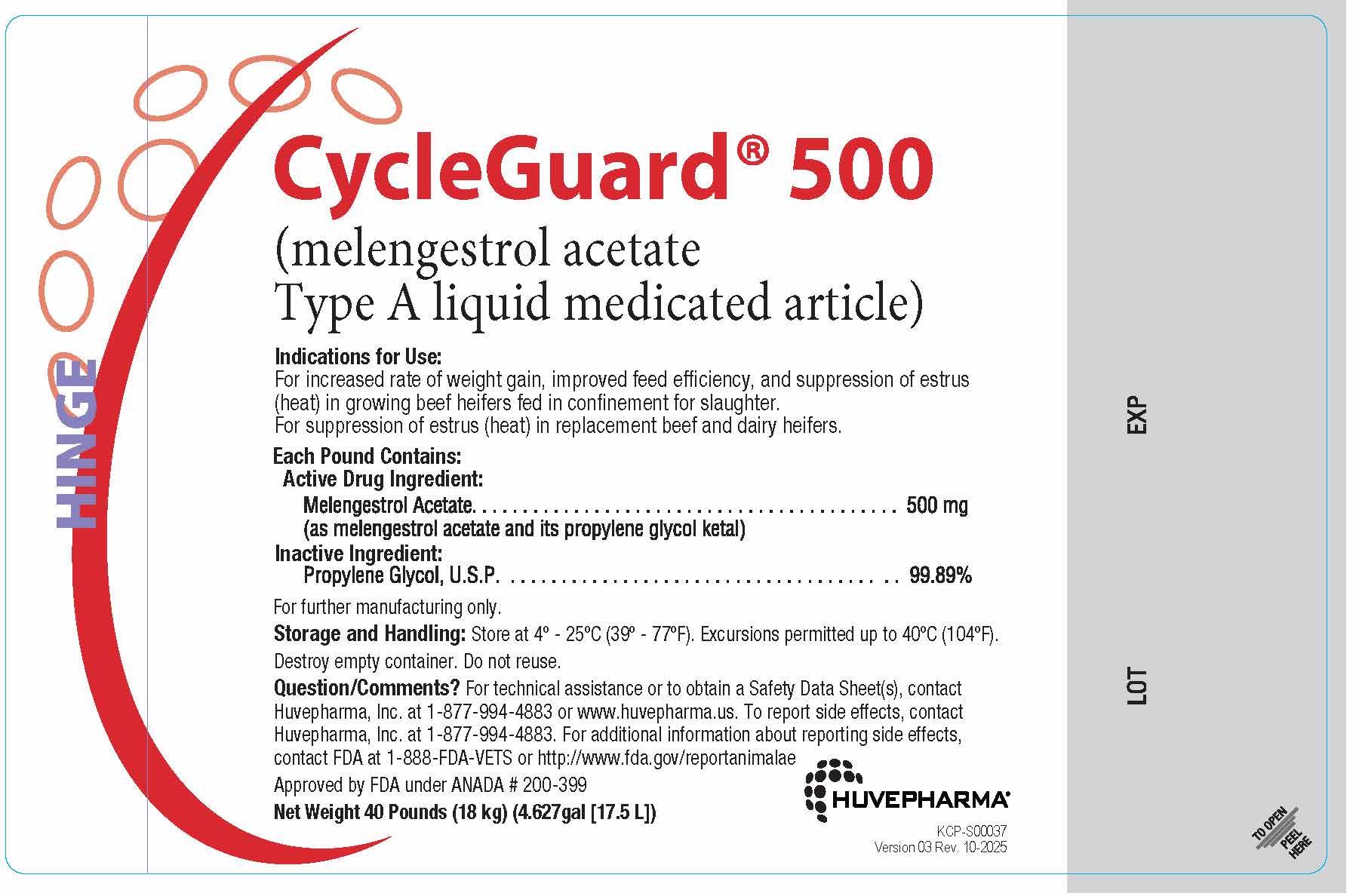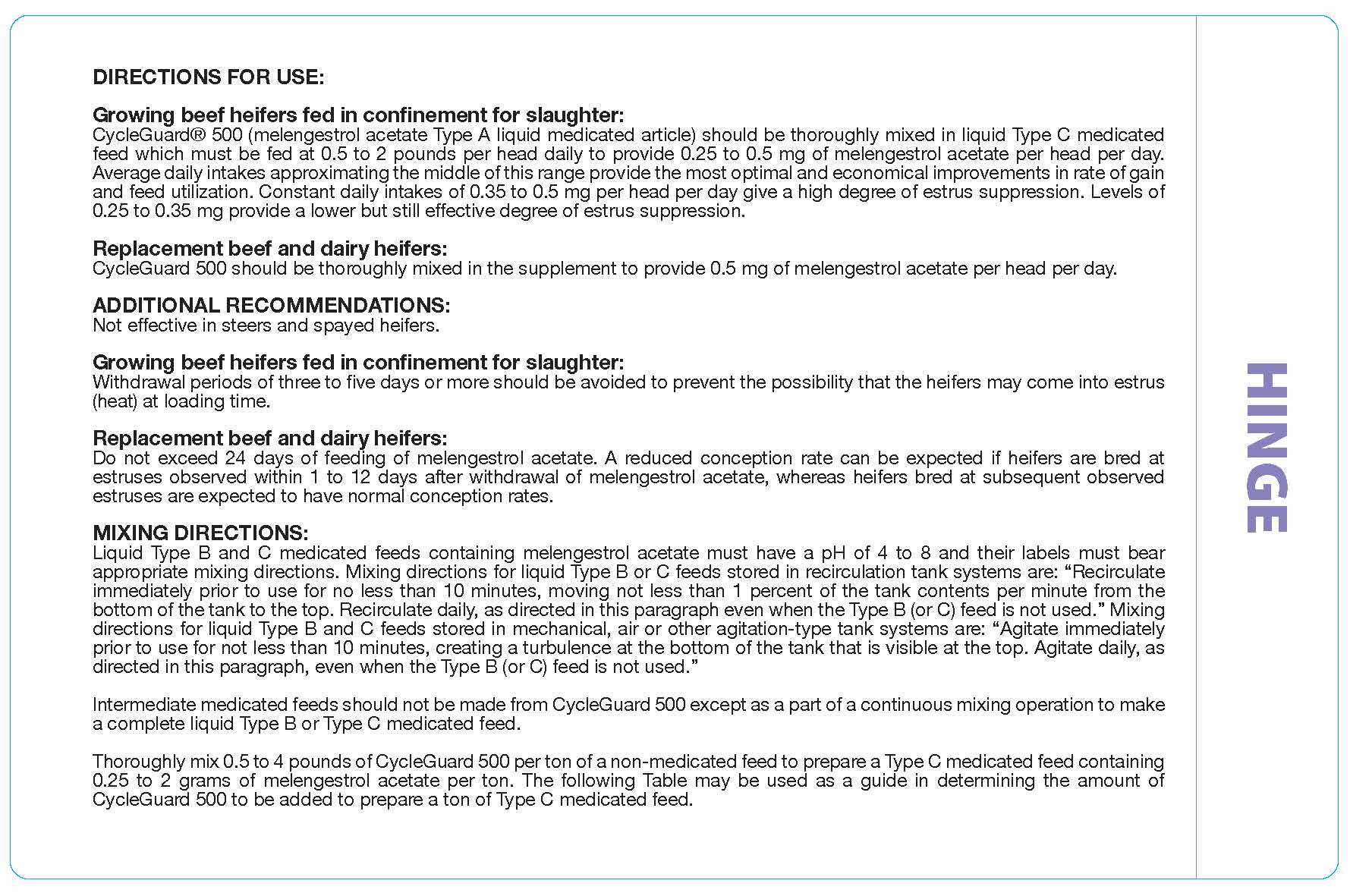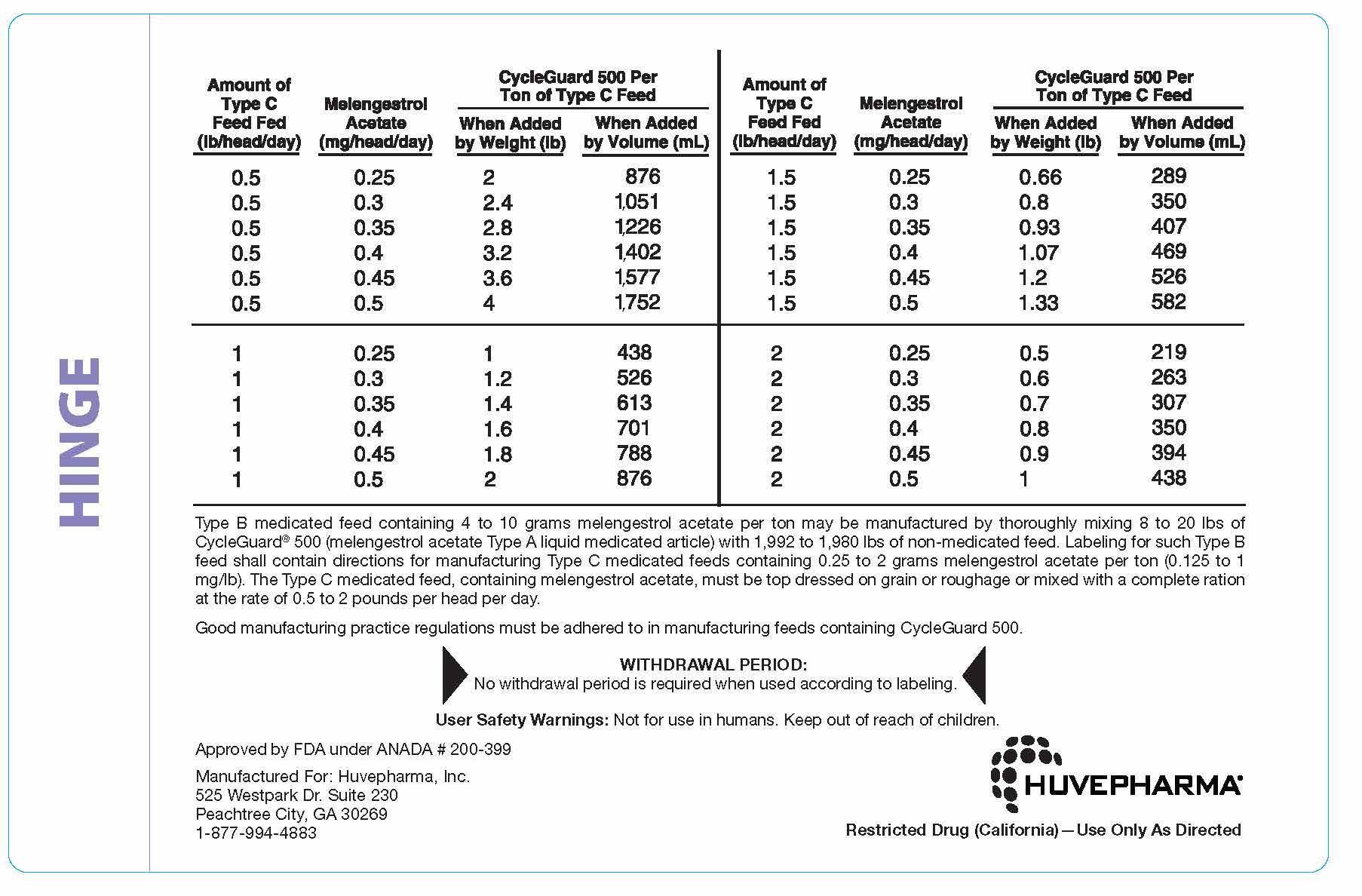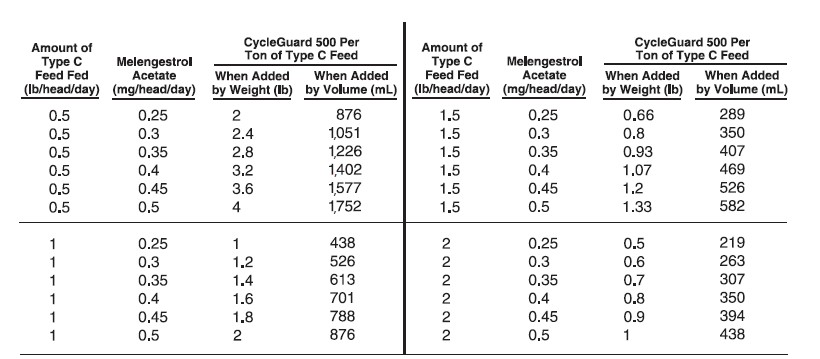 DRUG LABEL: CycleGuard
NDC: 23243-0068 | Form: LIQUID
Manufacturer: Huvepharma, Inc
Category: animal | Type: OTC TYPE A MEDICATED ARTICLE ANIMAL DRUG LABEL
Date: 20260106

ACTIVE INGREDIENTS: MELENGESTROL ACETATE 500 mg/.45 kg

CycleGuard® 500

(melengestrol acetate Type A liquid medicated article)

Indications for Use:
For increased rate of weight gain, improved feed effciency, and suppression of estrus
(heat) in growing beef heifers fed in confnement for slaughter.
For suppression of estrus (heat) in replacement beef and dairy heifers.

Each Pound Contains:
Active Drug Ingredient:
Melengestrol Acetate . . . . . . . . . . . . . . . . . . . . . . . . . . . . . . . . . . . . . . . . . . . 500 mg
(as melengestrol acetate and its propylene glycol ketal)
Inactive Ingredient:
Propylene Glycol, U.S.P. . . . . . . . . . . . . . . . . . . . . . . . . . . . . . . . . . . . . . . . . 99.89%

For further manufacturing only.

Storage and Handling: Store at 4º - 25ºC (39º - 77ºF). Excursions permitted up to 40ºC (104ºF).
Destroy empty container. Do not reuse.

ADVERSE REACTIONS

Question/Comments? For technical assistance or to obtain a Safety Data Sheet(s), contact
Huvepharma, Inc. at 1-877-994-4883 or www.huvepharma.us. To report side effects, contact
Huvepharma, Inc. at 1-877-994-4883. For additional information about reporting side effects,
contact FDA at 1-888-FDA-VETS or http://www.fda.gov/reportanimalae
Approved by FDA under ANADA # 200-399
Net Weight 40 Pounds (18 kg) (4.627gal [17.5 L])

INDICATIONS AND USAGE

DIRECTIONS FOR USE:

Growing beef heifers fed in confinement for slaughter:
CycleGuard® 500 (melengestrol acetate Type A liquid medicated article) should be thoroughly mixed in liquid Type C medicated
feed which must be fed at 0.5 to 2 pounds per head daily to provide 0.25 to 0.5 mg of melengestrol acetate per head per day.
Average daily intakes approximating the middle of this range provide the most optimal and economical improvements in rate of gain
and feed utilization. Constant daily intakes of 0.35 to 0.5 mg per head per day give a high degree of estrus suppression. Levels of
0.25 to 0.35 mg provide a lower but still effective degree of estrus suppression.

Replacement beef and dairy heifers:
CycleGuard 500 should be thoroughly mixed in the supplement to provide 0.5 mg of melengestrol acetate per head per day.

ADDITIONAL RECOMMENDATIONS:
Not effective in steers and spayed heifers.

Growing beef heifers fed in confinement for slaughter:
Withdrawal periods of three to five days or more should be avoided to prevent the possibility that the heifers may come into estrus
(heat) at loading time.

Replacement beef and dairy heifers:
Do not exceed 24 days of feeding of melengestrol acetate. A reduced conception rate can be expected if heifers are bred at
estruses observed within 1 to 12 days after withdrawal of melengestrol acetate, whereas heifers bred at subsequent observed
estruses are expected to have normal conception rates.

DOSAGE AND ADMINISTRATION

MIXING DIRECTIONS:
Liquid Type B and C medicated feeds containing melengestrol acetate must have a pH of 4 to 8 and their labels must bear
appropriate mixing directions. Mixing directions for liquid Type B or C feeds stored in recirculation tank systems are: “Recirculate
immediately prior to use for no less than 10 minutes, moving not less than 1 percent of the tank contents per minute from the
bottom of the tank to the top. Recirculate daily, as directed in this paragraph even when the Type B (or C) feed is not used.” Mixing
directions for liquid Type B and C feeds stored in mechanical, air or other agitation-type tank systems are: “Agitate immediately
prior to use for not less than 10 minutes, creating a turbulence at the bottom of the tank that is visible at the top. Agitate daily, as
directed in this paragraph, even when the Type B (or C) feed is not used.”

Intermediate medicated feeds should not be made from CycleGuard 500 except as a part of a continuous mixing operation to make
a complete liquid Type B or Type C medicated feed.

Thoroughly mix 0.5 to 4 pounds of CycleGuard 500 per ton of a non-medicated feed to prepare a Type C medicated feed containing
0.25 to 2 grams of melengestrol acetate per ton. The following Table may be used as a guide in determining the amount of
CycleGuard 500 to be added to prepare a ton of Type C medicated feed.

DOSAGE AND ADMINISTRATION

Type B medicated feed containing 4 to 10 grams melengestrol acetate per ton may be manufactured by thoroughly mixing 8 to 20 lbs of
CycleGuard® 500 (melengestrol acetate Type A liquid medicated article) with 1,992 to 1,980 lbs of non-medicated feed. Labeling for such Type B
feed shall contain directions for manufacturing Type C medicated feeds containing 0.25 to 2 grams melengestrol acetate per ton (0.125 to 1
mg/lb). The Type C medicated feed, containing melengestrol acetate, must be top dressed on grain or roughage or mixed with a complete ration
at the rate of 0.5 to 2 pounds per head per day.

Good manufacturing practice regulations must be adhered to in manufacturing feeds containing CycleGuard 500.

RESIDUE WARNING

WITHDRAWAL PERIOD:
No withdrawal period is required when used according to labeling.

User Safety Warnings: Not for use in humans. Keep out of reach of children.

Approved by FDA under ANADA #200-399

Manufactured For: Huvepharma, Inc.
525 Westpark Dr. Suite 230
Peachtree City, GA 30269
1-877-994-4883

Restricted Drug (California)—Use Only As Directed